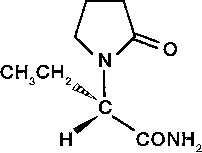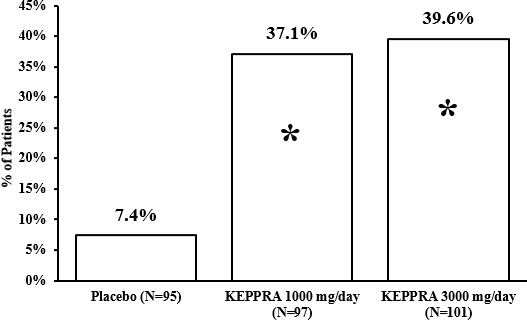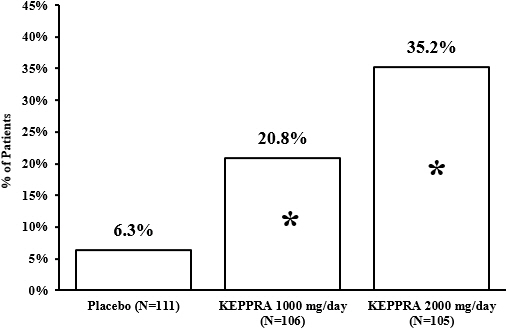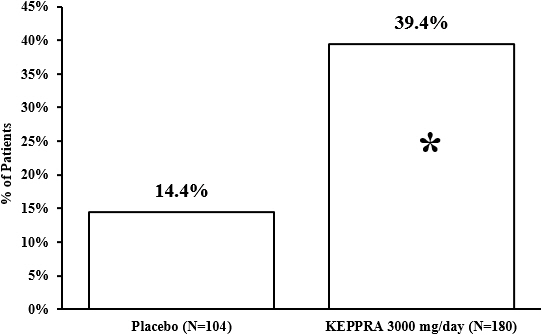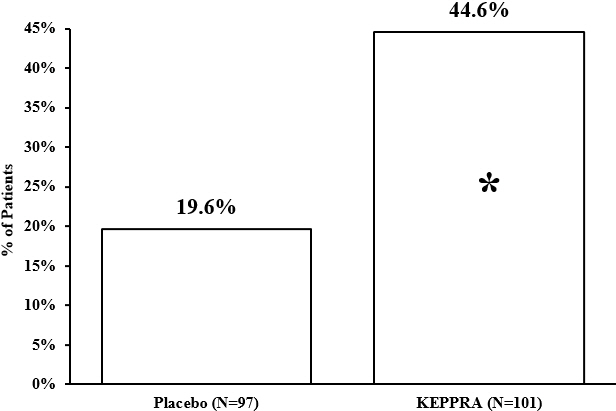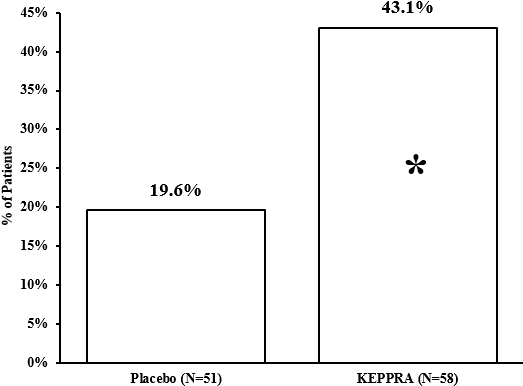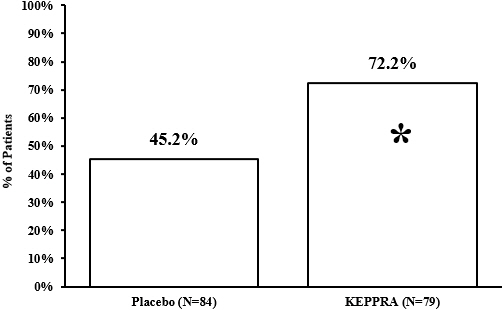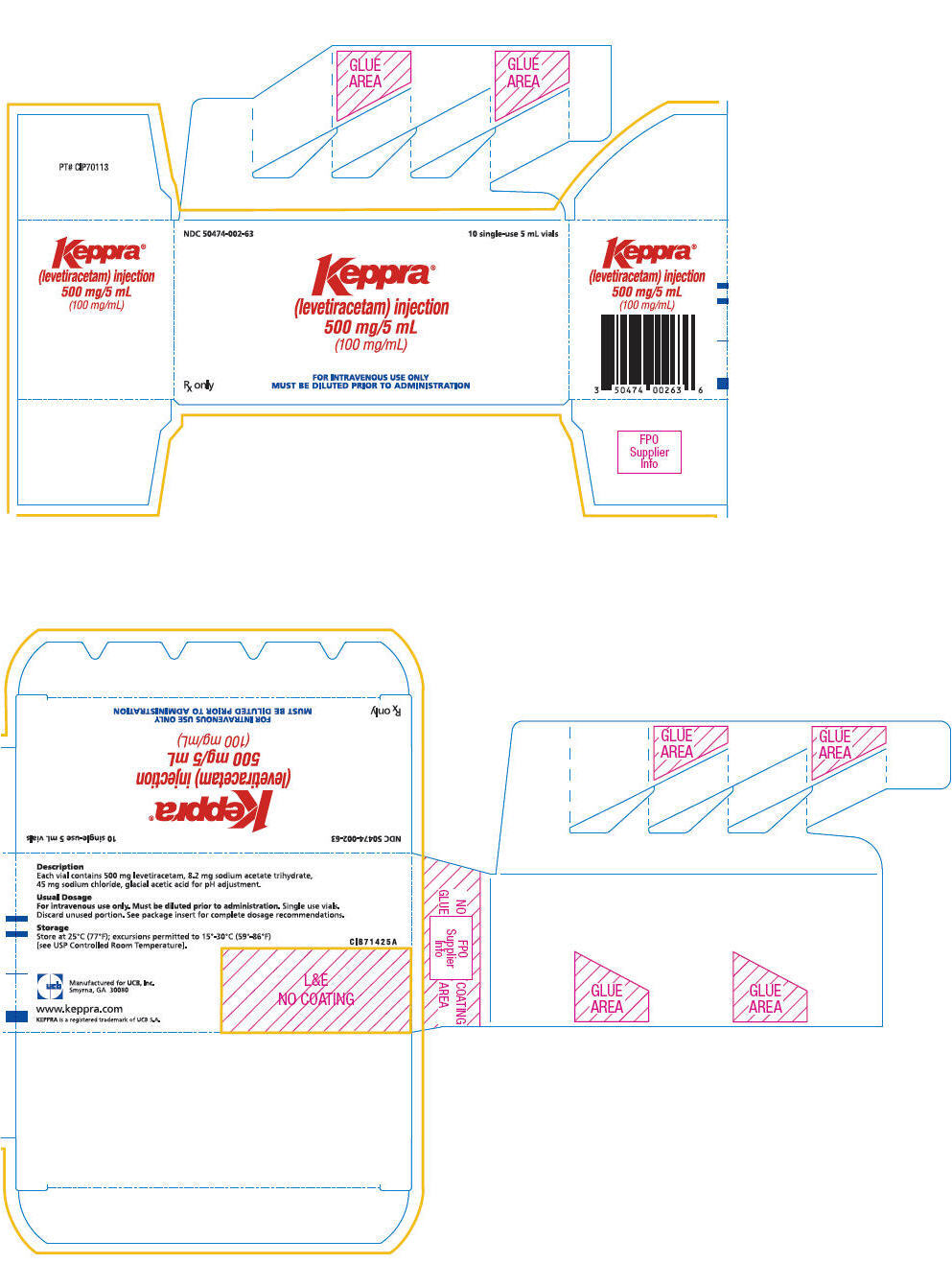 DRUG LABEL: Keppra
NDC: 50474-002 | Form: INJECTION, SOLUTION, CONCENTRATE
Manufacturer: UCB, Inc.
Category: prescription | Type: HUMAN PRESCRIPTION DRUG LABEL
Date: 20250630

ACTIVE INGREDIENTS: LEVETIRACETAM 100 mg/1 mL
INACTIVE INGREDIENTS: WATER; SODIUM CHLORIDE; ACETIC ACID; SODIUM ACETATE

HIGHLIGHTS OF PRESCRIBING INFORMATION

These highlights do not include all the information needed to use KEPPRA®safely and effectively. See full prescribing information for KEPPRA®.
KEPPRA®(levetiracetam) injection, for intravenous use
Initial U.S. Approval: 1999

RECENT MAJOR CHANGES

Warnings and Precautions (5.5) | 3/2024

1 INDICATIONS AND USAGE

- KEPPRA is indicated for the treatment of partial-onset seizures in patients 1 month of age and older (1.1)
- KEPPRA is indicated for adjunctive therapy for the treatment of:
  - Myoclonic seizures in patients 12 years of age and older with juvenile myoclonic epilepsy (1.2)
  - Primary generalized tonic-clonic seizures in patients 6 years of age and older with idiopathic generalized epilepsy (1.3)
- KEPPRA injection is for intravenous use only as an alternative for patients when oral administration is temporarily not feasible (1.4)

2 DOSAGE AND ADMINISTRATION

KEPPRA injection is for intravenous use only (2.1)

Partial-Onset Seizures (monotherapy or adjunctive therapy)

- 1 Month to < 6 Months: 7 mg/kg twice daily; increase by 7 mg/kg twice daily every 2 weeks to recommended dose of 21 mg/kg twice daily (2.1)
- 6 Months to < 4 Years: 10 mg/kg twice daily; increase by 10 mg/kg twice daily every 2 weeks to recommended dose of 25 mg/kg twice daily (2.1)
- 4 Years to < 16 Years: 10 mg/kg twice daily; increase by 10 mg/kg twice daily every 2 weeks to recommended dose of 30 mg/kg twice daily (2.1)
- Adults 16 Years and Older: 500 mg twice daily; increase by 500 mg twice daily every 2 weeks to a recommended dose of 1500 mg twice daily (2.1)

Myoclonic Seizures in Adults and Pediatric Patients 12 Years and Older

- 500 mg twice daily; increase by 500 mg twice daily every 2 weeks to recommended dose of 1500 mg twice daily (2.2)

Primary Generalized Tonic-Clonic Seizures

- 6 Years to < 16 Years: 10 mg/kg twice daily; increase by 10 mg/kg twice daily every 2 weeks to recommended dose of 30 mg/kg twice daily (2.3)
- Adults 16 Years and Older: 500 mg twice daily; increase by 500 mg twice daily every 2 weeks to recommended dose of 1500 mg twice daily (2.3)

Switching From or To Oral KEPPRA

When switching from or to oral KEPPRA, the total daily dosage/frequency of KEPPRA injection should be equivalent to those of oral KEPPRA (2.4, 2.5)

See full prescribing information for preparation and administration instructions (2.6) and dosage adjustment in adults with renal impairment (2.7)

3 DOSAGE FORMS AND STRENGTHS

Injection: 500 mg/5 mL single-use vial (3)

4 CONTRAINDICATIONS

Known hypersensitivity to levetiracetam; angioedema and anaphylaxis have occurred (4, 5.3)

5 WARNINGS AND PRECAUTIONS

- Behavioral abnormalities including psychotic symptoms, suicidal ideation, irritability, and aggressive behavior have been observed; monitor patients for psychiatric signs and symptoms (5.1)
- Monitor for somnolence and fatigue; advise patients not to drive or operate machinery until they have sufficient experience on KEPPRA (5.2)
- Serious Dermatological Reactions: Discontinue KEPPRA at the first sign of rash unless clearly not drug related (5.4)
- Drug Reaction with Eosinophilia and Systemic Symptoms (DRESS)/Multiorgan Hypersensitivity: Discontinue if no alternative etiology (5.5)
- Coordination Difficulties: Monitor for ataxia, abnormal gait, and incoordination (5.6)
- Withdrawal Seizures: KEPPRA must be gradually withdrawn (5.7)

6 ADVERSE REACTIONS

Most common adverse reactions (incidence ≥ 5% more than placebo) include:

- Adults: somnolence, asthenia, infection, and dizziness (6.1)
- Pediatric patients: fatigue, aggression, nasal congestion, decreased appetite, and irritability (6.1)

To report SUSPECTED ADVERSE REACTIONS, contact UCB, Inc. at (844) 599-CARE (2273) or FDA at 1-800-FDA-1088 or www.fda.gov/medwatch.

8 USE IN SPECIFIC POPULATIONS

Pregnancy: Plasma levels of levetiracetam may be decreased; monitor closely during pregnancy. Based on animal data, may cause fetal harm (5.10, 8.1)

FULL PRESCRIBING INFORMATION

1 INDICATIONS AND USAGE

1.1 Partial-Onset Seizures

KEPPRA is indicated for the treatment of partial-onset seizures in patients 1 month of age and older.

1.2 Myoclonic Seizures in Patients with Juvenile Myoclonic Epilepsy

KEPPRA is indicated as adjunctive therapy for the treatment of myoclonic seizures in patients 12 years of age and older with juvenile myoclonic epilepsy.

1.3 Primary Generalized Tonic-Clonic Seizures

KEPPRA is indicated as adjunctive therapy for the treatment of primary generalized tonic-clonic seizures in patients 6 years of age and older with idiopathic generalized epilepsy.

1.4 Limitations of Use

KEPPRA injection is for intravenous use only as an alternative for patients when oral administration is temporarily not feasible.

2 DOSAGE AND ADMINISTRATION

2.1 Dosing for Partial-Onset Seizures

The recommended dosing for monotherapy and adjunctive therapy is the same as outlined below.

There is no clinical study experience with administration of intravenous levetiracetam for a period longer than 4 days.

Adults 16 Years of Age and Older

Initiate treatment with a daily dose of 1000 mg/day, given as twice-daily dosing (500 mg twice daily). Additional dosing increments may be given (1000 mg/day additional every 2 weeks) to a maximum recommended daily dose of 3000 mg. There is no evidence that doses greater than 3000 mg/day confer additional benefit.

Pediatric Patients

1 Month to < 6 Months

Initiate treatment with a daily dose of 14 mg/kg in 2 divided doses (7 mg/kg twice daily). Increase the daily dose every 2 weeks by increments of 14 mg/kg to the recommended daily dose of 42 mg/kg (21 mg/kg twice daily). In the clinical trial, the mean daily dose was 35 mg/kg in this age group.

6 Months to < 4 Years

Initiate treatment with a daily dose of 20 mg/kg in 2 divided doses (10 mg/kg twice daily). Increase the daily dose in 2 weeks by an increment of 20 mg/kg to the recommended daily dose of 50 mg/kg (25 mg/kg twice daily). If a patient cannot tolerate a daily dose of 50 mg/kg, the daily dose may be reduced. In the clinical trial, the mean daily dose was 47 mg/kg in this age group.

4 Years to < 16 Years

Initiate treatment with a daily dose of 20 mg/kg in 2 divided doses (10 mg/kg twice daily). Increase the daily dose every 2 weeks by increments of 20 mg/kg to the recommended daily dose of 60 mg/kg (30 mg/kg twice daily). If a patient cannot tolerate a daily dose of 60 mg/kg, the daily dose may be reduced. In the clinical trial, the mean daily dose was 44 mg/kg. The maximum daily dose was 3000 mg/day.

2.2 Dosing for Myoclonic Seizures in Patients with Juvenile Myoclonic Epilepsy

Initiate treatment with a dose of 1000 mg/day, given as twice-daily dosing (500 mg twice daily). Increase the dosage by 1000 mg/day every 2 weeks to the recommended daily dose of 3000 mg. The effectiveness of doses lower than 3000 mg/day has not been studied.

2.3 Dosing for Primary Generalized Tonic-Clonic Seizures

Adults 16 Years of Age and Older

Initiate treatment with a dose of 1000 mg/day, given as twice-daily dosing (500 mg twice daily). Increase dosage by 1000 mg/day every 2 weeks to the recommended daily dose of 3000 mg. The effectiveness of doses lower than 3000 mg/day has not been adequately studied.

Pediatric Patients 6 to <16 Years of Age

Initiate treatment with a daily dose of 20 mg/kg in 2 divided doses (10 mg/kg twice daily). Increase the daily dose every 2 weeks by increments of 20 mg/kg (10 mg/kg twice daily) to the recommended daily dose of 60 mg/kg (30 mg/kg twice daily). The effectiveness of doses lower than 60 mg/kg/day has not been adequately studied.

2.4 Switching from Oral Dosing

When switching from oral KEPPRA, the initial total daily intravenous dosage of KEPPRA should be equivalent to the total daily dosage and frequency of oral KEPPRA.

2.5 Switching to Oral Dosing

At the end of the intravenous treatment period, the patient may be switched to KEPPRA oral administration at the equivalent daily dosage and frequency of the intravenous administration.

2.6 Preparation and Administration Instructions

KEPPRA injection is for intravenous use only and should be diluted in 100 mL of a compatible diluent prior to administration. If a smaller volume is required (e.g. pediatric patients), the amount of diluent should be calculated to not exceed a maximum levetiracetam concentration of 15 mg per mL of diluted solution. Consideration should also be given to the total daily fluid intake of the patient. KEPPRA injection should be administered as a 15-minute IV infusion. One vial of KEPPRA injection contains 500 mg levetiracetam (500 mg/5 mL).

KEPPRA injection may be mixed with the following diluents and antiepileptic drugs and may be stored in polyvinyl chloride (PVC) bags. The diluted solution should not be stored for more than 4 hours at controlled room temperature [15-30°C (59-86°F)].

Diluents:
Sodium chloride (0.9%) injection, USP
Lactated Ringer's injection
Dextrose 5% injection, USP

Other Antiepileptic Drugs:
Lorazepam
Diazepam
Valproate sodium

There are no data to support the physical compatibility of KEPPRA injection with antiepileptic drugs that are not listed above.

Parenteral drug products should be inspected visually for particulate matter and discoloration prior to administration whenever solution and container permit. Product with particulate matter or discoloration should not be used.

Any unused portion of the KEPPRA injection vial contents should be discarded.

Adults

See Table 1for the recommended preparation and administration of KEPPRA injection for adults to achieve a dose of 500 mg, 1000 mg, or 1500 mg.

Table 1: Preparation and Administration of KEPPRA Injection for Adults
Dose | Withdraw Volume | Volume of Diluent | Infusion Time
500 mg | 5 mL (5 mL vial) | 100 mL | 15 minutes
1000 mg | 10 mL (two 5 mL vials) | 100 mL | 15 minutes
1500 mg | 15 mL (three 5 mL vials) | 100 mL | 15 minutes

For example, to prepare a 1000 mg dose, dilute 10 mL of KEPPRA injection in 100 mL of a compatible diluent and administer intravenously as a 15-minute infusion.

Pediatric Patients

When using KEPPRA injection for pediatric patients, dosing is weight-based (mg per kg).

The following calculation should be used to determine the appropriate daily dose of KEPPRA injection for pediatric patients:

Total daily dose (mL/day) = | Daily dose (mg/kg/day) × patient weight (kg) ------------------------------------------------
 | 100 mg/mL

2.7 Dosage Adjustments in Adult Patients with Renal Impairment

KEPPRA dosing must be individualized according to the patient's renal function status. Recommended dosage adjustments for adults with renal impairment are shown in Table 2. Information is unavailable for dosage adjustments in pediatric patients with renal impairment. In order to calculate the dose recommended for adult patients with renal impairment, creatinine clearance adjusted for body surface area must be calculated. To do this an estimate of the patient's creatinine clearance (CLcr) in mL/min must first be calculated using the following formula:

CLcr= | [140-age (years)] × weight (kg) ----------------------------------- 72 × serum creatinine (mg/dL) | (× 0.85 for female patients)

Then CLcr is adjusted for body surface area (BSA) as follows:

CLcr (mL/min/1.73m^2)= | CLcr (mL/min) ---------------------------× 1.73 BSA subject (m^2)

Table 2: Dosage Adjustment Regimen for Adult Patients with Renal Impairment
Group | Creatinine Clearance (mL/min/1.73m^2) | Dosage (mg) | Frequency
Normal | > 80 | 500 to 1,500 | Every 12 hours
Mild | 50 – 80 | 500 to 1,000 | Every 12 hours
Moderate | 30 – 50 | 250 to 750 | Every 12 hours
Severe | < 30 | 250 to 500 | Every 12 hours
ESRD patients using dialysis | ------- | 500 to 1,000 [Following dialysis, a 250 to 500 mg supplemental dose is recommended.] | Every 24 hours

2.8 Discontinuation of KEPPRA

Avoid abrupt withdrawal from KEPPRA in order to reduce the risk of increased seizure frequency and status epilepticus [see Warnings and Precautions (5.7)] .

3 DOSAGE FORMS AND STRENGTHS

One vial of KEPPRA injection contains 500 mg levetiracetam (500 mg/5 mL) as a clear, colorless solution.

4 CONTRAINDICATIONS

KEPPRA is contraindicated in patients with a hypersensitivity to levetiracetam .Reactions have included anaphylaxis and angioedema [see Warnings and Precautions (5.3)] .

5 WARNINGS AND PRECAUTIONS

5.1 Behavioral Abnormalities and Psychotic Symptoms

KEPPRA may cause behavioral abnormalities and psychotic symptoms. Patients treated with KEPPRA should be monitored for psychiatric signs and symptoms.

Behavioral abnormalities

In clinical studies using an oral formulation of KEPPRA, 13% of adult KEPPRA-treated patients and 38% of pediatric KEPPRA-treated patients (4 to 16 years of age), compared to 6% and 19% of adult and pediatric placebo-treated patients, experienced non-psychotic behavioral symptoms (reported as aggression, agitation, anger, anxiety, apathy, depersonalization, depression, emotional lability, hostility, hyperkinesias, irritability, nervousness, neurosis, and personality disorder).

A randomized, double-blind, placebo-controlled study was performed to assess the neurocognitive and behavioral effects of an oral formulation of KEPPRA as adjunctive therapy in pediatric patients (4 to 16 years of age). The results from an exploratory analysis indicated a worsening in KEPPRA-treated patients on aggressive behavior (one of eight behavior dimensions), as measured in a standardized and systematic way using a validated instrument, the Achenbach Child Behavior Checklist (CBCL/6-18).

In clinical studies in pediatric patients 1 month to < 4 years of age, irritability was reported in 12% of the KEPPRA-treated patients compared to 0% of placebo-treated patients.

In clinical studies, 1.7% of adult KEPPRA-treated patients discontinued treatment due to behavioral adverse reactions, compared to 0.2% of placebo-treated patients. The treatment dose was reduced in 0.8% of adult KEPPRA-treated patients and in 0.5% of placebo-treated patients. Overall, 11% of KEPPRA-treated pediatric patients experienced behavioral symptoms associated with discontinuation or dose reduction, compared to 6% of placebo-treated patients.

Psychotic symptoms

In clinical studies using an oral formulation of KEPPRA, 1% of KEPPRA-treated adult patients, 2% of KEPPRA-treated pediatric patients 4 to 16 years of age, and 17% of KEPPRA-treated pediatric patients 1 month to <4 years of age experienced psychotic symptoms, compared to 0.2%, 2%, and 5% in the corresponding age groups treated with placebo. In a controlled study that assessed the neurocognitive and behavioral effects of an oral formulation of KEPPRA in pediatric patients 4 to 16 years of age, 1.6% of KEPPRA-treated patients experienced paranoia, compared to 0% of placebo-treated patients. In the same study, 3.1% of KEPPRA-treated patients experienced confusional state, compared to 0% of placebo-treated patients [see Use in Specific Populations (8.4)] .

In clinical studies, two (0.3%) KEPPRA-treated adult patients were hospitalized, and their treatment was discontinued due to psychosis. Both events, reported as psychosis, developed within the first week of treatment and resolved within 1 to 2 weeks following treatment discontinuation. There was no difference between drug- and placebo-treated patients in the incidence of the pediatric patients who discontinued treatment due to psychotic and non-psychotic adverse reactions.

5.2 Somnolence and Fatigue

KEPPRA may cause somnolence and fatigue. Patients should be monitored for somnolence and fatigue, and be advised not to drive or operate machinery until they have gained sufficient experience on KEPPRA to gauge whether it adversely affects their ability to drive or operate machinery.

Somnolence

In controlled clinical studies using an oral formulation of KEPPRA in adult patients with partial-onset seizures, 15% of KEPPRA-treated patients reported somnolence, compared to 8% of placebo-treated patients. There was no clear dose response up to 3000 mg/day. In a study in which there was no titration, about 45% of patients receiving KEPPRA 4000 mg/day reported somnolence. The somnolence was considered serious in 0.3% of KEPPRA-treated patients, compared to 0% in the placebo group. About 3% of KEPPRA-treated patients discontinued treatment due to somnolence, compared to 0.7% of placebo-treated patients. In 1.4% of KEPPRA-treated patients and 0.9% of placebo-treated patients, the dose was reduced, while 0.3% of the KEPPRA-treated patients were hospitalized due to somnolence.

Asthenia

In controlled clinical studies using an oral formulation of KEPPRA in adult patients with partial-onset seizures, 15% of KEPPRA-treated patients reported asthenia, compared to 9% of placebo-treated patients. Treatment was discontinued due to asthenia in 0.8% of KEPPRA-treated patients as compared to 0.5% of placebo-treated patients. In 0.5% of KEPPRA-treated patients and in 0.2% of placebo-treated patients, the dose was reduced due to asthenia.

Somnolence and asthenia occurred most frequently within the first 4 weeks of treatment. In general, the incidences of somnolence and fatigue in the pediatric partial-onset seizure studies, and in pediatric and adult myoclonic and primary generalized tonic-clonic studies were comparable to those of the adult partial-onset seizure studies.

5.3 Anaphylaxis and Angioedema

KEPPRA can cause anaphylaxis or angioedema after the first dose or at any time during treatment. Signs and symptoms in cases reported in the postmarketing setting have included hypotension, hives, rash, respiratory distress, and swelling of the face, lip, mouth, eye, tongue, throat, and feet. In some reported cases, reactions were life-threatening and required emergency treatment. If a patient develops signs or symptoms of anaphylaxis or angioedema, KEPPRA should be discontinued and the patient should seek immediate medical attention. KEPPRA should be discontinued permanently if a clear alternative etiology for the reaction cannot be established [see Contraindications (4)] .

5.4 Serious Dermatological Reactions

Serious dermatological reactions, including Stevens-Johnson syndrome (SJS) and toxic epidermal necrolysis (TEN), have been reported in both pediatric and adult patients treated with KEPPRA. The median time of onset is reported to be 14 to 17 days, but cases have been reported at least four months after initiation of treatment. Recurrence of the serious skin reactions following rechallenge with KEPPRA has also been reported. KEPPRA should be discontinued at the first sign of a rash, unless the rash is clearly not drug-related. If signs or symptoms suggest SJS/TEN, use of this drug should not be resumed and alternative therapy should be considered.

5.5 Drug Reaction with Eosinophilia and Systemic Symptoms (DRESS)/Multiorgan Hypersensitivity

Drug Reaction with Eosinophilia and Systemic Symptoms (DRESS), also known as multiorgan hypersensitivity, has been reported in patients taking antiepileptic drugs, including KEPPRA. These events can be fatal or life-threatening, particularly if diagnosis and treatment do not occur as early as possible. DRESS typically, although not exclusively, presents with fever, rash, lymphadenopathy, and/or facial swelling, in association with other organ system involvement, such as hepatitis, nephritis, hematological abnormalities, myocarditis, or myositis, sometimes resembling an acute viral infection. Eosinophilia is often present. Because this disorder is variable in its expression, other organ systems not noted here may be involved. It is important to note that early manifestations of hypersensitivity, such as fever or lymphadenopathy, may be present even though rash is not evident. If such signs or symptoms are present, the patient should be evaluated immediately. KEPPRA should be discontinued if an alternative etiology for the signs or symptoms cannot be established [see Contraindications (4)] .

5.6 Coordination Difficulties

KEPPRA may cause coordination difficulties.

In controlled clinical studies using an oral formulation of KEPPRA in adult patients with partial-onset seizures, 3.4% of KEPPRA-treated patients experienced coordination difficulties, (reported as ataxia, abnormal gait, or incoordination) compared to 1.6% of placebo-treated patients. A total of 0.4% of patients in controlled clinical studies discontinued KEPPRA treatment due to ataxia, compared to 0% of placebo-treated patients. In 0.7% of KEPPRA-treated patients and in 0.2% of placebo-treated patients, the dose was reduced due to coordination difficulties, while one of the treated patients was hospitalized due to worsening of pre-existing ataxia. These events occurred most frequently within the first 4 weeks of treatment.

Patients should be monitored for signs and symptoms of coordination difficulties and advised not to drive or operate machinery until they have gained sufficient experience on KEPPRA to gauge whether it could adversely affect their ability to drive or operate machinery.

5.7 Withdrawal Seizures

As with most antiepileptic drugs, KEPPRA should generally be withdrawn gradually because of the risk of increased seizure frequency and status epilepticus. But if withdrawal is needed because of a serious adverse reaction, rapid discontinuation can be considered.

5.8 Hematologic Abnormalities

KEPPRA can cause hematologic abnormalities. Hematologic abnormalities occurred in clinical trials and included decreases in white blood cell (WBC), neutrophil, and red blood cells counts (RBC); decreases in hemoglobin and hematocrit; and increases in eosinophil counts. Cases of agranulocytosis, pancytopenia, and thrombocytopenia have been reported in the postmarketing setting. A complete blood count is recommended in patients experiencing significant weakness, pyrexia, recurrent infections, or coagulation disorders.

Partial-Onset Seizures

Adults

In controlled clinical studies using an oral formulation of KEPPRA in adult patients with partial-onset seizures, minor but statistically significant decreases compared to placebo in total mean RBC (0.03 × 10^6/mm^3), mean hemoglobin (0.09 g/dL), and mean hematocrit (0.38%), were seen in KEPPRA-treated patients.

A total of 3.2% of KEPPRA-treated and 1.8% of placebo-treated patients had at least one possibly significant (≤2.8 × 10^9/L) decreased WBC, and 2.4% of KEPPRA-treated and 1.4% of placebo-treated patients had at least one possibly significant (≤1.0 × 10^9/L) decreased neutrophil count. Of the KEPPRA-treated patients with a low neutrophil count, all but one rose towards or to baseline with continued treatment. No patient was discontinued secondary to low neutrophil counts.

Pediatric Patients 4 Years to < 16 Years

In a controlled study in pediatric patients age 4 years to <16 years, statistically significant decreases in WBC and neutrophil counts were seen in KEPPRA-treated patients, as compared to placebo. The mean decreases from baseline in the KEPPRA-treated group were -0.4 × 10^9/L and -0.3 × 10^9/L, respectively, whereas there were small increases in the placebo group. Mean relative lymphocyte counts increased by 1.7% in KEPPRA-treated patients, compared to a decrease of 4% in placebo-treated patients (statistically significant).

More KEPPRA-treated patients had a possibly clinically significant abnormally low WBC value (3% of KEPPRA-treated patients versus 0% of placebo-treated patients); however, there was no apparent difference between treatment groups with respect to neutrophil count (5% on KEPPRA versus 4.2% on placebo). No patient was discontinued because of low WBC or neutrophil count.

In a randomized, double-blind, placebo-controlled study to assess the neurocognitive and behavioral effects of an oral formulation of KEPPRA as adjunctive therapy in pediatric patients (4 to 16 years of age), 5 patients (8.6%) in the KEPPRA-treated group and two patients (6.1%) in the placebo-treated group had high eosinophil count values that were possibly clinically significant (≥10% or ≥0.7 × 10^9/L).

5.9 Increase in Blood Pressure

In a randomized, placebo-controlled study in patients 1 month to <4 years of age using an oral formulation of KEPPRA, a significantly higher risk of increased diastolic blood pressure was observed in the KEPPRA-treated patients (17%), compared to placebo-treated patients (2%). There was no overall difference in mean diastolic blood pressure between the treatment groups. This disparity between the KEPPRA and placebo treatment groups was not observed in the studies of older children or in adults.

Monitor patients 1 month to <4 years of age for increases in diastolic blood pressure.

5.10 Seizure Control During Pregnancy

Physiological changes may gradually decrease plasma levels of levetiracetam throughout pregnancy. This decrease is more pronounced during the third trimester. It is recommended that patients be monitored carefully during pregnancy. Close monitoring should continue through the postpartum period especially if the dose was changed during pregnancy.

6 ADVERSE REACTIONS

The following adverse reactions are discussed in more details in other sections of labeling:

- Behavioral Abnormalities and Psychotic Symptoms [see Warnings and Precautions (5.1)]
- Somnolence and Fatigue [see Warnings and Precautions (5.2)]
- Anaphylaxis and Angioedema [see Warnings and Precautions (5.3)]
- Serious Dermatological Reactions [see Warnings and Precautions (5.4)]
- Drug Reaction with Eosinophilia and Systemic Symptoms (DRESS)/Multiorgan Hypersensitivity [see Warnings and Precautions (5.5)]
- Coordination Difficulties [see Warnings and Precautions (5.6)]
- Hematologic Abnormalities [see Warnings and Precautions (5.8)]
- Increase in Blood Pressure [see Warnings and Precautions (5.9)]

6.1 Clinical Trials Experience

Because clinical trials are conducted under widely varying conditions, adverse reaction rates observed in the clinical trials of a drug cannot be directly compared to rates in the clinical trials of another drug and may not reflect the rates observed in practice.

The adverse reactions that result from KEPPRA injection use include all of those reported for KEPPRA tablets and oral solution. Equivalent doses of intravenous (IV) levetiracetam and oral levetiracetam result in equivalent Cmax, Cmin, and total systemic exposure to levetiracetam when the IV levetiracetam is administered as a 15-minute infusion.

Partial-Onset Seizures

Adults

In controlled clinical studies using KEPPRA tablets in adults with partial-onset seizures [see Clinical Studies (14.1)], the most common adverse reactions in adult patients receiving KEPPRA in combination with other AEDs, for events with rates greater than placebo, were somnolence, asthenia, infection, and dizziness. Of the most common adverse reactions in adults experiencing partial-onset seizures, asthenia, somnolence, and dizziness occurred predominantly during the first 4 weeks of treatment with KEPPRA.

Table 3 lists adverse reactions that occurred in at least 1% of adult epilepsy patients receiving KEPPRA tablets in placebo-controlled studies and were numerically more common than in patients treated with placebo. In these studies, either KEPPRA or placebo was added to concurrent AED therapy.

Table 3: Adverse Reactions [Adverse reactions occurred in at least 1% of KEPPRA-treated patients and occurred more frequently than placebo-treated patients] in Pooled Placebo-Controlled, Adjunctive Studies in Adults Experiencing Partial-Onset Seizures
 | KEPPRA (N=769) % | Placebo (N=439) %
Asthenia | 15 | 9
Somnolence | 15 | 8
Headache | 14 | 13
Infection | 13 | 8
Dizziness | 9 | 4
Pain | 7 | 6
Pharyngitis | 6 | 4
Depression | 4 | 2
Nervousness | 4 | 2
Rhinitis | 4 | 3
Anorexia | 3 | 2
Ataxia | 3 | 1
Vertigo | 3 | 1
Amnesia | 2 | 1
Anxiety | 2 | 1
Cough Increased | 2 | 1
Diplopia | 2 | 1
Emotional Lability | 2 | 0
Hostility | 2 | 1
Paresthesia | 2 | 1
Sinusitis | 2 | 1

In controlled adult clinical studies using KEPPRA tablets, 15% of patients receiving KEPPRA and 12% receiving placebo either discontinued or had a dose reduction as a result of an adverse reaction. Table 4 lists the most common (>1%) adverse reactions that resulted in discontinuation or dose reduction and that occurred more frequently in KEPPRA-treated patients than in placebo-treated patients.

Table 4: Adverse Reactions that Resulted in Discontinuation or Dose Reduction in Pooled Placebo-Controlled Studies in Adults Experiencing Partial-Onset Seizures
Adverse Reaction | KEPPRA (N=769) % | Placebo (N=439) %
Somnolence | 4 | 2
Dizziness | 1 | 0

Pediatric Patients 4 Years to <16 Years

The adverse reaction data presented below was obtained from a pooled analysis of two controlled pediatric clinical studies using an oral formulation in pediatric patients 4 to 16 years of age with partial-onset seizures. The most common adverse reactions in pediatric patients receiving KEPPRA in combination with other AEDs, for events with rates greater than placebo, were fatigue, aggression, nasal congestion, decreased appetite, and irritability.

Table 5 lists adverse reactions from the pooled pediatric controlled studies (4 to 16 years of age) that occurred in at least 2% of pediatric KEPPRA-treated patients and were numerically more common than in pediatric patients treated with placebo. In these studies, either KEPPRA or placebo was added to concurrent AED therapy.

Table 5: Adverse Reactions [Adverse reactions occurred in at least 2% of pediatric KEPPRA-treated patients and occurred more frequently than placebo-treated patients] in Pooled Placebo-Controlled, Adjunctive Studies in Pediatric Patients Ages 4 to 16 Years Experiencing Partial-Onset Seizures
 | KEPPRA (N=165) % | Placebo (N=131) %
Headache | 19 | 15
Nasopharyngitis | 15 | 12
Vomiting | 15 | 12
Somnolence | 13 | 9
Fatigue | 11 | 5
Aggression | 10 | 5
Upper Abdominal Pain | 9 | 8
Cough | 9 | 5
Nasal Congestion | 9 | 2
Decreased Appetite | 8 | 2
Abnormal Behavior | 7 | 4
Dizziness | 7 | 5
Irritability | 7 | 1
Pharyngolaryngeal Pain | 7 | 4
Diarrhea | 6 | 2
Lethargy | 6 | 5
Insomnia | 5 | 3
Agitation | 4 | 1
Anorexia | 4 | 3
Head Injury | 4 | 0
Constipation | 3 | 1
Contusion | 3 | 1
Depression | 3 | 1
Fall | 3 | 2
Influenza | 3 | 1
Mood Altered | 3 | 1
Affect Lability | 2 | 1
Anxiety | 2 | 1
Arthralgia | 2 | 0
Confusional State | 2 | 0
Conjunctivitis | 2 | 0
Ear Pain | 2 | 1
Gastroenteritis | 2 | 0
Joint Sprain | 2 | 1
Mood Swings | 2 | 1
Neck Pain | 2 | 1
Rhinitis | 2 | 0
Sedation | 2 | 1

In the controlled pooled pediatric clinical studies in patients 4-16 years of age, 7% of patients receiving KEPPRA and 9% receiving placebo discontinued as a result of an adverse reaction.

Pediatric Patients 1 Month to < 4 Years

In the 7-day controlled pediatric clinical study using an oral formulation of KEPPRA in children 1 month to less than 4 years of age with partial-onset seizures, the most common adverse reactions in patients receiving KEPPRA in combination with other AEDs, for events with rates greater than placebo, were somnolence and irritability. Because of the shorter exposure period, incidences of adverse reactions are expected to be lower than in other pediatric studies in older patients. Therefore, other controlled pediatric data, presented above, should also be considered to apply to this age group.

Table 6 lists adverse reactions that occurred in at least 5% of pediatric epilepsy patients (ages 1 month to < 4 years) treated with KEPPRA in the placebo-controlled study and were numerically more common than in patients treated with placebo. In this study, either KEPPRA or placebo was added to concurrent AED therapy.

Table 6: Adverse Reactions [Adverse reactions occurred in at least 5% of KEPPRA-treated patients and occurred more frequently than placebo-treated patients] in a Placebo-Controlled, Adjunctive Study in Pediatric Patients Ages 1 Month to < 4 Years Experiencing Partial-Onset Seizures
 | KEPPRA (N=60) % | Placebo (N=56) %
Somnolence | 13 | 2
Irritability | 12 | 0

In the 7-day controlled pediatric clinical study in patients 1 month to < 4 years of age, 3% of patients receiving KEPPRA and 2% receiving placebo either discontinued or had a dose reduction as a result of an adverse reaction. There was no adverse reaction that resulted in discontinuation for more than one patient.

Myoclonic Seizures

Although the pattern of adverse reactions in this study seems somewhat different from that seen in patients with partial-onset seizures, this is likely due to the much smaller number of patients in this study compared to partial seizure studies. The adverse reaction pattern for patients with JME is expected to be essentially the same as for patients with partial seizures.

In the controlled clinical study using KEPPRA tablets in patients with myoclonic seizures [see Clinical Studies (14.2)] , the most common adverse reactions in patients receiving KEPPRA in combination with other AEDs, for events with rates greater than placebo, were somnolence, neck pain, and pharyngitis.

Table 7 lists adverse reactions that occurred in at least 5% of juvenile myoclonic epilepsy patients experiencing myoclonic seizures treated with KEPPRA tablets and were numerically more common than in patients treated with placebo. In this study, either KEPPRA or placebo was added to concurrent AED therapy.

Table 7: Adverse Reactions [Adverse reactions occurred in at least 5% of KEPPRA-treated patients and occurred more frequently than placebo-treated patients] in a Placebo-Controlled, Adjunctive Study in Patients 12 Years of Age and Older with Myoclonic Seizures
 | KEPPRA (N=60) % | Placebo (N=60) %
Somnolence | 12 | 2
Neck pain | 8 | 2
Pharyngitis | 7 | 0
Depression | 5 | 2
Influenza | 5 | 2
Vertigo | 5 | 3

In the placebo-controlled study using KEPPRA tablets in patients with JME, 8% of patients receiving KEPPRA and 2% receiving placebo either discontinued or had a dose reduction as a result of an adverse reaction. The adverse reactions that led to discontinuation or dose reduction and that occurred more frequently in KEPPRA-treated patients than in placebo-treated patients are presented in Table 8.

Table 8: Adverse Reactions that Resulted in Discontinuation or Dose Reduction in Patients with Juvenile Myoclonic Epilepsy
Adverse Reaction | KEPPRA (N=60) % | Placebo (N=60) %
Anxiety | 3 | 2
Depressed mood | 2 | 0
Depression | 2 | 0
Diplopia | 2 | 0
Hypersomnia | 2 | 0
Insomnia | 2 | 0
Irritability | 2 | 0
Nervousness | 2 | 0
Somnolence | 2 | 0

Primary Generalized Tonic-Clonic Seizures

Although the pattern of adverse reactions in this study seems somewhat different from that seen in patients with partial seizures, this is likely due to the much smaller number of patients in this study compared to partial seizure studies. The adverse reaction pattern for patients with primary generalized tonic-clonic (PGTC) seizures is expected to be essentially the same as for patients with partial seizures.

In the controlled clinical study that included patients 4 years of age and older with PGTC seizures, the most common adverse reaction in patients receiving KEPPRA oral formulation in combination with other AEDs, for events with rates greater than placebo was nasopharyngitis.

Table 9 lists adverse reactions that occurred in at least 5% of idiopathic generalized epilepsy patients experiencing PGTC seizures treated with KEPPRA and were numerically more common than in patients treated with placebo. In this study, either KEPPRA or placebo was added to concurrent AED therapy.

Table 9: Adverse Reactions [Adverse reactions occurred in at least 5% of KEPPRA-treated patients and occurred more frequently than placebo-treated patients] in a Placebo-Controlled, Adjunctive Study in Patients 4 Years of Age and Older with PGTC Seizures
 | KEPPRA (N=79) % | Placebo (N=84) %
Nasopharyngitis | 14 | 5
Fatigue | 10 | 8
Diarrhea | 8 | 7
Irritability | 6 | 2
Mood swings | 5 | 1

In the placebo-controlled study, 5% of patients receiving KEPPRA and 8% receiving placebo either discontinued or had a dose reduction during the treatment period as a result of an adverse reaction.

This study was too small to adequately characterize the adverse reactions that could be expected to result in discontinuation of treatment in this population. It is expected that the adverse reactions that would lead to discontinuation in this population would be similar to those resulting in discontinuation in other epilepsy trials (see tables 4and 8).

In addition, the following adverse reactions were seen in other controlled adult studies of KEPPRA: balance disorder, disturbance in attention, eczema, memory impairment, myalgia, and blurred vision.

Comparison of Gender, Age and Race

The overall adverse reaction profile of KEPPRA was similar between females and males. There are insufficient data to support a statement regarding the distribution of adverse reactions by age and race.

6.2 Postmarketing Experience

The following adverse reactions have been identified during postapproval use of KEPPRA. Because these reactions are reported voluntarily from a population of uncertain size, it is not always possible to reliably estimate their frequency or establish a causal relationship to drug exposure.

The following adverse reactions have been reported in patients receiving KEPPRA worldwide. The listing is alphabetized: abnormal liver function test, acute kidney injury, anaphylaxis, angioedema, agranulocytosis, choreoathetosis, drug reaction with eosinophilia and systemic symptoms (DRESS), dyskinesia, erythema multiforme, hepatic failure, hepatitis, hyponatremia, muscular weakness, obsessive-compulsive disorders (OCD), pancreatitis, pancytopenia (with bone marrow suppression identified in some of these cases), panic attack, thrombocytopenia, weight loss, and worsening of seizures including in patients with SCN8A mutations. Alopecia has been reported with KEPPRA use; recovery was observed in majority of cases where KEPPRA was discontinued.

8 USE IN SPECIFIC POPULATIONS

8.1 Pregnancy

Pregnancy Exposure Registry

There is a pregnancy exposure registry that monitors pregnancy outcomes in women exposed to antiepileptic drugs (AEDs), including KEPPRA, during pregnancy. Encourage women who are taking KEPPRA during pregnancy to enroll in the North American Antiepileptic Drug (NAAED) pregnancy registry by calling 1-888-233-2334 or visiting http://www.aedpregnancyregistry.org/.

Risk Summary

Prolonged experience with KEPPRA in pregnant women has not identified a drug-associated risk of major birth defects or miscarriage, based on published literature, which includes data from pregnancy registries, and reflects experience over two decades [see Human Data] . In animal studies, levetiracetam produced developmental toxicity (increased embryofetal and offspring mortality, increased incidences of fetal structural abnormalities, decreased embryofetal and offspring growth, neurobehavioral alterations in offspring) at doses similar to human therapeutic doses [see Animal Data] .

In the U.S. general population, the estimated background risk of major birth defects and miscarriage in clinically recognized pregnancies is 2-4% and 15-20%, respectively. The background risk of major birth defects and miscarriage for the indicated population is unknown.

Clinical Considerations

Levetiracetam blood levels may decrease during pregnancy [see Warnings and Precautions (5.10)].

Physiological changes during pregnancy may affect levetiracetam concentration. Decrease in levetiracetam plasma concentrations has been observed during pregnancy. This decrease is more pronounced during the third trimester. Dose adjustments may be necessary to maintain clinical response.

Data

Human Data

While available studies cannot definitively establish the absence of risk, data from the published literature and pregnancy registries have not established an association with levetiracetam use during pregnancy and major birth defects or miscarriage.

Animal Data

When levetiracetam (0, 400, 1200, or 3600 mg/kg/day) was administered orally to pregnant rats during the period of organogenesis, reduced fetal weights and increased incidence of fetal skeletal variations were observed at the highest dose tested. There was no evidence of maternal toxicity. The no-effect dose for adverse effects on embryofetal developmental in rats (1200 mg/kg/day) is approximately 4 times the maximum recommended human dose (MRHD) of 3000 mg on a body surface area (mg/m^2) basis.

Oral administration of levetiracetam (0, 200, 600, or 1800 mg/kg/day) to pregnant rabbits during the period of organogenesis resulted in increased embryofetal mortality and incidence of fetal skeletal variations at the mid and high dose and decreased fetal weights and increased incidence of fetal malformations at the high dose, which was associated with maternal toxicity. The no-effect dose for adverse effects on embryofetal development in rabbits (200 mg/kg/day) is approximately equivalent to the MRHD on a mg/m2 basis.

Oral administration of levetiracetam (0, 70, 350, or 1800 mg/kg/day) to female rats throughout pregnancy and lactation led to an increased incidence of fetal skeletal variations, reduced fetal body weight, and decreased growth in offspring at the mid and high doses and increased pup mortality and neurobehavioral alterations in offspring at the highest dose tested. There was no evidence of maternal toxicity. The no-effect dose for adverse effects on pre- and postnatal development in rats (70 mg/kg/day) is less than the MRHD on a mg/m2 basis.

Oral administration of levetiracetam to rats during the latter part of gestation and throughout lactation produced no adverse developmental or maternal effects at doses of up to 1800 mg/kg/day (6 times the MRHD on a mg/m2 basis).

8.2 Lactation

Risk Summary

Levetiracetam is excreted in human milk. There are no data on the effects of KEPPRA on the breastfed infant, or the effects on milk production.

The developmental and health benefits of breastfeeding should be considered along with the mother's clinical need for KEPPRA and any potential adverse effects on the breastfed infant from KEPPRA or from the underlying maternal condition.

8.4 Pediatric Use

The safety and effectiveness of KEPPRA for the treatment of partial-onset seizures in patients 1 month to 16 years of age have been established [see Clinical Pharmacology (12.3)and Clinical Studies (14.1)] . The dosing recommendation in these pediatric patients varies according to age group and is weight-based [see Dosage and Administration (2.6)] .

The safety and effectiveness of KEPPRA as adjunctive therapy for the treatment of myoclonic seizures in adolescents 12 years of age and older with juvenile myoclonic epilepsy have been established [see Clinical Studies (14.2)] .

The safety and effectiveness of KEPPRA as adjunctive therapy for the treatment of primary generalized tonic-clonic seizures in pediatric patients 6 years of age and older with idiopathic generalized epilepsy have been established [see Clinical Studies (14.3)] .

Safety and effectiveness for the treatment of partial-onset seizures in pediatric patients below the age of 1 month; adjunctive therapy for the treatment of myoclonic seizures in pediatric patients below the age of 12 years; and adjunctive therapy for the treatment of primary generalized tonic-clonic seizures in pediatric patients below the age of 6 years have not been established.

A 3-month, randomized, double-blind, placebo-controlled study was performed to assess the neurocognitive and behavioral effects of KEPPRA as adjunctive therapy in 98 (KEPPRA N=64, placebo N=34) pediatric patients, ages 4 years to 16 years, with partial seizures that were inadequately controlled. The target dose was 60 mg/kg/day .Neurocognitive effects were measured by the Leiter-R Attention and Memory (AM) Battery, which measures various aspects of a child's memory and attention. Although no substantive differences were observed between the placebo and drug treated groups in the median change from baseline in this battery, the study was not adequate to assess formal statistical non-inferiority of the drug and placebo. The Achenbach Child Behavior Checklist (CBCL/6-18), a standardized validated tool used to assess a child's competencies and behavioral/emotional problems, was also assessed in this study. An analysis of the CBCL/6-18 indicated, on average, a worsening in KEPPRA-treated patients in aggressive behavior, one of the eight syndrome scores [see Warnings and Precautions (5.1)] .

Juvenile Animal Toxicity Data

Studies of levetiracetam in juvenile rats (dosed on postnatal days 4 through 52) and dogs (dosed from postnatal weeks 3 through 7) at doses of up to 1800 mg/kg/day (approximately 7 and 24 times, respectively, the maximum recommended pediatric dose of 60 mg/kg/day on a mg/m^2basis) did not demonstrate adverse effects on postnatal development.

8.5 Geriatric Use

There were 347 subjects in clinical studies of levetiracetam that were 65 years old and over. No overall differences in safety were observed between these subjects and younger subjects. There were insufficient numbers of elderly subjects in controlled trials of epilepsy to adequately assess the effectiveness of KEPPRA in these patients.

Levetiracetam is known to be substantially excreted by the kidney, and the risk of adverse reactions to this drug may be greater in patients with impaired renal function. Because elderly patients are more likely to have decreased renal function, care should be taken in dose selection, and it may be useful to monitor renal function [see Clinical Pharmacology (12.3)] .

8.6 Renal Impairment

Clearance of levetiracetam is decreased in patients with renal impairment and is correlated with creatinine clearance [see Clinical Pharmacology (12.3)] . Dosage adjustment is recommended for patients with impaired renal function and supplemental doses should be given to patients after dialysis [see Dosage and Administration (2.7)] .

10 OVERDOSAGE

10.1 Signs, Symptoms and Laboratory Findings of Acute Overdosage in Humans

The highest known dose of oral KEPPRA received in the clinical development program was 6000 mg/day. Other than drowsiness, there were no adverse reactions in the few known cases of overdose in clinical trials. Cases of somnolence, agitation, aggression, depressed level of consciousness, respiratory depression, and coma were observed with KEPPRA overdoses in postmarketing use.

10.2 Management of Overdose

There is no specific antidote for overdose with KEPPRA. If indicated, elimination of unabsorbed drug should be attempted by emesis or gastric lavage; usual precautions should be observed to maintain airway. General supportive care of the patient is indicated including monitoring of vital signs and observation of the patient's clinical status. A Certified Poison Control Center should be contacted for up to date information on the management of overdose with KEPPRA.

10.3 Hemodialysis

Standard hemodialysis procedures result in significant clearance of levetiracetam (approximately 50% in 4 hours) and should be considered in cases of overdose. Although hemodialysis has not been performed in the few known cases of overdose, it may be indicated by the patient's clinical state or in patients with significant renal impairment.

11 DESCRIPTION

KEPPRA injection is an antiepileptic drug available as a clear, colorless, sterile solution (100 mg/mL) for intravenous administration.

The chemical name of levetiracetam, a single enantiomer, is (-)-(S)-α-ethyl-2-oxo-1-pyrrolidine acetamide, its molecular formula is C8H14N2O2 and its molecular weight is 170.21. Levetiracetam is chemically unrelated to existing antiepileptic drugs (AEDs). It has the following structural formula:

Levetiracetam is a white to off-white crystalline powder with a faint odor and a bitter taste. It is very soluble in water (104.0 g/100 mL). It is freely soluble in chloroform (65.3 g/100 mL) and in methanol (53.6 g/100 mL), soluble in ethanol (16.5 g/100 mL), sparingly soluble in acetonitrile (5.7 g/100 mL) and practically insoluble in n-hexane. (Solubility limits are expressed as g/100 mL solvent.)

KEPPRA injection contains 100 mg of levetiracetam per mL. It is supplied in single-use 5 mL vials containing 500 mg levetiracetam, water for injection, 45 mg sodium chloride, and buffered at approximately pH 5.5 with glacial acetic acid and 8.2 mg sodium acetate trihydrate. KEPPRA injection must be diluted prior to intravenous infusion [see Dosage and Administration (2.6)] .

12 CLINICAL PHARMACOLOGY

12.1 Mechanism of Action

The precise mechanism(s) by which levetiracetam exerts its antiepileptic effect is unknown.

A saturable and stereoselective neuronal binding site in rat brain tissue has been described for levetiracetam. Experimental data indicate that this binding site is the synaptic vesicle protein SV2A, thought to be involved in the regulation of vesicle exocytosis. Although the molecular significance of levetiracetam binding to synaptic vesicle protein SV2A is not understood, levetiracetam and related analogs showed a rank order of affinity for SV2A which correlated with the potency of their antiseizure activity in audiogenic seizure-prone mice. These findings suggest that the interaction of levetiracetam with the SV2A protein may contribute to the antiepileptic mechanism of action of the drug.

12.2 Pharmacodynamics

Effects on QTc Interval

The effect of KEPPRA on QTc prolongation was evaluated in a randomized, double-blind, positive-controlled (moxifloxacin 400 mg) and placebo-controlled crossover study of KEPPRA (1000 mg or 5000 mg) in 52 healthy subjects. The upper bound of the 90% confidence interval for the largest placebo-adjusted, baseline-corrected QTc was below 10 milliseconds. Therefore, there was no evidence of significant QTc prolongation in this study.

12.3 Pharmacokinetics

Equivalent doses of intravenous (IV) levetiracetam and oral levetiracetam result in equivalent Cmax, Cmin, and total systemic exposure to levetiracetam when the IV levetiracetam is administered as a 15-minute infusion.

Overview

Levetiracetam is rapidly and almost completely absorbed after oral administration. Levetiracetam injection and tablets are bioequivalent. The pharmacokinetics of levetiracetam are linear and time-invariant, with low intra- and inter-subject variability. Levetiracetam is not significantly protein-bound (<10% bound) and its volume of distribution is close to the volume of intracellular and extracellular water. Sixty-six percent (66%) of the dose is renally excreted unchanged. The major metabolic pathway of levetiracetam (24% of dose) is an enzymatic hydrolysis of the acetamide group. It is not liver cytochrome P450 dependent. The metabolites have no known pharmacological activity and are renally excreted. Plasma half-life of levetiracetam across studies is approximately 6-8 hours. It is increased in the elderly (primarily due to impaired renal clearance) and in subjects with renal impairment.

The pharmacokinetics of levetiracetam are similar when used as monotherapy or as adjunctive therapy for the treatment of partial-onset seizures.

Distribution

The equivalence of levetiracetam injection and the oral formulation was demonstrated in a bioavailability study of 17 healthy volunteers. In this study, levetiracetam 1500 mg was diluted in 100 mL 0.9% sterile saline solution and was infused over 15 minutes. The selected infusion rate provided plasma concentrations of levetiracetam at the end of the infusion period similar to those achieved at Tmaxafter an equivalent oral dose. It is demonstrated that levetiracetam 1500 mg intravenous infusion is equivalent to levetiracetam 3 × 500 mg oral tablets. The time independent pharmacokinetic profile of levetiracetam was demonstrated following 1500 mg intravenous infusion for 4 days with BID dosing. The AUC(0-12)at steady-state was equivalent to AUCinffollowing an equivalent single dose.

Levetiracetam and its major metabolite are less than 10% bound to plasma proteins; clinically significant interactions with other drugs through competition for protein binding sites are therefore unlikely.

Metabolism

Levetiracetam is not extensively metabolized in humans. The major metabolic pathway is the enzymatic hydrolysis of the acetamide group, which produces the carboxylic acid metabolite, ucb L057 (24% of dose) and is not dependent on any liver cytochrome P450 isoenzymes. The major metabolite is inactive in animal seizure models. Two minor metabolites were identified as the product of hydroxylation of the 2-oxo-pyrrolidine ring (2% of dose) and opening of the 2-oxo-pyrrolidine ring in position 5 (1% of dose). There is no enantiomeric interconversion of levetiracetam or its major metabolite.

Elimination

Levetiracetam plasma half-life in adults is 7 ± 1 hour and is unaffected by either dose, route of administration or repeated administration. Levetiracetam is eliminated from the systemic circulation by renal excretion as unchanged drug which represents 66% of administered dose. The total body clearance is 0.96 mL/min/kg and the renal clearance is 0.6 mL/min/kg. The mechanism of excretion is glomerular filtration with subsequent partial tubular reabsorption. The metabolite ucb L057 is excreted by glomerular filtration and active tubular secretion with a renal clearance of 4 mL/min/kg. Levetiracetam elimination is correlated to creatinine clearance. Levetiracetam clearance is reduced in patients with renal impairment [see Dosage and Administration (2.6)and Use in Specific Populations (8.6)] .

Specific Populations

Elderly

Pharmacokinetics of levetiracetam were evaluated in 16 elderly subjects (age 61-88 years) with creatinine clearance ranging from 30 to 74 mL/min. Following oral administration of twice-daily dosing for 10 days, total body clearance decreased by 38% and the half-life was 2.5 hours longer in the elderly compared to healthy adults. This is most likely due to the decrease in renal function in these subjects.

Pediatric Patients

- Intravenous Formulation
  A population pharmacokinetic analysis for the intravenous formulation was conducted in 49 pediatric patients (1 month to < 16 years of age) weighing 3-79 kg. Patients received levetiracetam as a 15-minute IV infusion at doses between 14 mg/kg/day and 60 mg/kg/day twice daily. Plasma concentrations and model derived steady-state exposure AUC (0-12) were within the range of the exposure observed in pediatric patients receiving equivalent doses of the oral solution.

- Oral Formulations
  Pharmacokinetics of levetiracetam were evaluated in 24 pediatric patients (age 6-12 years) after single oral dose (20 mg/kg) of the immediate release formulation of KEPPRA. The body weight adjusted apparent clearance of levetiracetam was approximately 40% higher than in adults.
  A repeat dose pharmacokinetic study was conducted in pediatric patients (age 4-12 years) at doses of 20 mg/kg/day, 40 mg/kg/day, and 60 mg/kg/day of the immediate release formulation of KEPPRA. The evaluation of the pharmacokinetic profile of levetiracetam and its metabolite (ucb L057) in 14 pediatric patients demonstrated rapid absorption of levetiracetam at all doses, with a Tmaxof about 1 hour and a t1/2of 5 hours across all dosing levels. The pharmacokinetics of levetiracetam in pediatric patients was linear between 20 to 60 mg/kg/day. The potential interaction of levetiracetam with other AEDs was also evaluated in these patients. Levetiracetam had no significant effect on the plasma concentrations of carbamazepine, valproic acid, topiramate or lamotrigine. However, there was about a 22% increase of apparent clearance of levetiracetam when it was co-administered with an enzyme-inducing AED (e.g., carbamazepine).
  Following single dose administration (20 mg/kg) of a 10% oral solution to pediatric patients with epilepsy (1 month to < 4 years), levetiracetam was rapidly absorbed and peak plasma concentrations were observed approximately 1 hour after dosing. Levetiracetam half-life in pediatric patients 1 month to < 4 years with epilepsy was shorter (5.3 h) than in adults (7.2 h), and apparent clearance (1.5 mL/min/kg) was faster than in adults (0.96 mL/min/kg).
  Population pharmacokinetic analysis showed that body weight was significantly correlated to the clearance of levetiracetam in pediatric patients; clearance increased with an increase in body weight.

Pregnancy

Levetiracetam levels may decrease during pregnancy [see Warnings and Precautions (5.10)and Use in Specific Populations (8.1)] .

Gender

Levetiracetam Cmaxand AUC were 20% higher in women (N=11) compared to men (N=12). However, clearances adjusted for body weight were comparable.

Race

Formal pharmacokinetic studies of the effects of race have not been conducted. Cross-study comparisons involving Caucasians (N=12) and Asians (N=12), however, show that pharmacokinetics of levetiracetam were comparable between the two races. Because levetiracetam is primarily renally excreted and there are no important racial differences in creatinine clearance, pharmacokinetic differences due to race are not expected.

Renal Impairment

The disposition of levetiracetam was studied in adult subjects with varying degrees of renal function. Total body clearance of levetiracetam is reduced in patients with impaired renal function by 40% in the mild group (CLcr = 50-80 mL/min), 50% in the moderate group (CLcr = 30-50 mL/min) and 60% in the severe renal impairment group (CLcr <30 mL/min). Clearance of levetiracetam is correlated with creatinine clearance.

In anuric (end stage renal disease) patients, the total body clearance decreased 70% compared to normal subjects (CLcr >80mL/min). Approximately 50% of the pool of levetiracetam in the body is removed during a standard 4 hour hemodialysis procedure [see Dosage and Administration (2.7)] .

Hepatic Impairment

In subjects with mild (Child-Pugh A) to moderate (Child-Pugh B) hepatic impairment, the pharmacokinetics of levetiracetam were unchanged. In patients with severe hepatic impairment (Child-Pugh C), total body clearance was 50% that of normal subjects, but decreased renal clearance accounted for most of the decrease. No dose adjustment is needed for patients with hepatic impairment.

Drug Interactions

In vitrodata on metabolic interactions indicate that levetiracetam is unlikely to produce, or be subject to, pharmacokinetic interactions. Levetiracetam and its major metabolite, at concentrations well above Cmaxlevels achieved within the therapeutic dose range, are neither inhibitors of, nor high affinity substrates for, human liver cytochrome P450 isoforms, epoxide hydrolase or UDP-glucuronidation enzymes. In addition, levetiracetam does not affect the in vitroglucuronidation of valproic acid.

Potential pharmacokinetic interactions of or with levetiracetam were assessed in clinical pharmacokinetic studies (phenytoin, valproate, warfarin, digoxin, oral contraceptive, probenecid) and through pharmacokinetic screening in the placebo-controlled clinical studies in epilepsy patients.

Phenytoin

KEPPRA (3000 mg daily) had no effect on the pharmacokinetic disposition of phenytoin in patients with refractory epilepsy. Pharmacokinetics of levetiracetam were also not affected by phenytoin.

Valproate

KEPPRA (1500 mg twice daily) did not alter the pharmacokinetics of valproate in healthy volunteers. Valproate 500 mg twice daily did not modify the rate or extent of levetiracetam absorption or its plasma clearance or urinary excretion. There also was no effect on exposure to and the excretion of the primary metabolite, ucb L057.

Other Antiepileptic Drugs

Potential drug interactions between KEPPRA and other AEDs (carbamazepine, gabapentin, lamotrigine, phenobarbital, phenytoin, primidone and valproate) were also assessed by evaluating the serum concentrations of levetiracetam and these AEDs during placebo-controlled clinical studies. These data indicate that levetiracetam does not influence the plasma concentration of other AEDs and that these AEDs do not influence the pharmacokinetics of levetiracetam.

Effect of AEDs in Pediatric Patients

There was about a 22% increase of apparent total body clearance of levetiracetam when it was co-administered with enzyme-inducing AEDs. Dose adjustment is not recommended. Levetiracetam had no effect on plasma concentrations of carbamazepine, valproate, topiramate, or lamotrigine.

Oral Contraceptives

KEPPRA (500 mg twice daily) did not influence the pharmacokinetics of an oral contraceptive containing 0.03 mg ethinyl estradiol and 0.15 mg levonorgestrel, or of the luteinizing hormone and progesterone levels, indicating that impairment of contraceptive efficacy is unlikely. Coadministration of this oral contraceptive did not influence the pharmacokinetics of levetiracetam.

Digoxin

KEPPRA (1000 mg twice daily) did not influence the pharmacokinetics and pharmacodynamics (ECG) of digoxin given as a 0.25 mg dose every day. Coadministration of digoxin did not influence the pharmacokinetics of levetiracetam.

Warfarin

KEPPRA (1000 mg twice daily) did not influence the pharmacokinetics of R and S warfarin. Prothrombin time was not affected by levetiracetam. Coadministration of warfarin did not affect the pharmacokinetics of levetiracetam.

Probenecid

Probenecid, a renal tubular secretion blocking agent, administered at a dose of 500 mg four times a day, did not change the pharmacokinetics of levetiracetam 1000 mg twice daily. Cssmaxof the metabolite, ucb L057, was approximately doubled in the presence of probenecid while the fraction of drug excreted unchanged in the urine remained the same. Renal clearance of ucb L057 in the presence of probenecid decreased 60%, probably related to competitive inhibition of tubular secretion of ucb L057. The effect of KEPPRA on probenecid was not studied.

13 NONCLINICAL TOXICOLOGY

13.1 Carcinogenesis, Mutagenesis, Impairment of Fertility

Carcinogenesis

Rats were dosed with levetiracetam in the diet for 104 weeks at doses of 50, 300, and 1800 mg/kg/day. Plasma exposure (AUC) at the highest dose was approximately 6 times that in humans at the maximum recommended human dose (MRHD) of 3000 mg. There was no evidence of carcinogenicity. In mice, oral administration of levetiracetam for 80 weeks (doses up to 960 mg/kg/day) or 2 years (doses up to 4000 mg/kg/day, lowered to 3000 mg/kg/day after 45 weeks due to intolerability) was not associated with an increase in tumors. The highest dose tested in mice for 2 years (3000 mg/kg/day) is approximately 5 times the MRHD on a body surface area (mg/m^2) basis.

Mutagenesis

Levetiracetam was negative in in vitro(Ames, chromosomal aberration in mammalian cells) and in vivo(mouse micronucleus) assays. The major human metabolite of levetiracetam (ucb L057) was negative in in vitro(Ames ,mouse lymphoma) assays.

Impairment of Fertility

No adverse effects on male or female fertility or reproductive performance were observed in rats at oral doses up to 1800 mg/kg/day, which were associated with plasma exposures (AUC) up to approximately 6 times that in humans at the MRHD.

14 CLINICAL STUDIES

All clinical studies supporting the efficacy of KEPPRA utilized oral formulations. The finding of efficacy of KEPPRA injection is based on the results of studies using an oral formulation of KEPPRA, and on the demonstration of comparable bioavailability of the oral and parenteral formulations [see Clinical Pharmacology (12.3)] .

14.1 Partial-Onset Seizures

Effectiveness in Partial-Onset Seizures in Adults

The effectiveness of KEPPRA for the treatment of partial-onset seizures in adults was established in three multicenter, randomized, double-blind, placebo-controlled clinical studies in patients who had refractory partial-onset seizures with or without secondary generalization. The tablet formulation was used in all these studies. In these studies, 904 patients were randomized to placebo, 1000 mg, 2000 mg, or 3000 mg/day. Patients enrolled in Study 1 or Study 2 had refractory partial-onset seizures for at least two years and had taken two or more classical AEDs. Patients enrolled in Study 3 had refractory partial-onset seizures for at least 1 year and had taken one classical AED. At the time of the study, patients were taking a stable dose regimen of at least one and could take a maximum of two AEDs. During the baseline period, patients had to have experienced at least two partial-onset seizures during each 4-week period.

Study 1

Study 1 was a double-blind, placebo-controlled, parallel-group study conducted at 41 sites in the United States comparing KEPPRA 1000 mg/day (N=97), KEPPRA 3000 mg/day (N=101), and placebo (N=95) given in equally divided doses twice daily. After a prospective baseline period of 12 weeks, patients were randomized to one of the three treatment groups described above. The 18-week treatment period consisted of a 6-week titration period, followed by a 12-week fixed dose evaluation period, during which concomitant AED regimens were held constant. The primary measure of effectiveness was a between group comparison of the percent reduction in weekly partial seizure frequency relative to placebo over the entire randomized treatment period (titration + evaluation period). Secondary outcome variables included the responder rate (incidence of patients with ≥50% reduction from baseline in partial-onset seizure frequency). The results of the analysis of Study 1 are displayed in Table 10.

Table 10: Reduction in Mean Over Placebo in Weekly Frequency of Partial-Onset Seizures in Study 1
 | Placebo (N=95) | KEPPRA 1000 mg/day (N=97) | KEPPRA 3000 mg/day (N=101)
Percent reduction in partial seizure frequency over placebo | – | 26.1% [statistically significant versus placebo] | 30.1%

The percentage of patients (y-axis) who achieved ≥50% reduction in weekly seizure rates from baseline in partial-onset seizure frequency over the entire randomized treatment period (titration + evaluation period) within the three treatment groups (x-axis) is presented in Figure 1.

Figure 1: Responder Rate (≥50% Reduction from Baseline) in Study 1

* statistically significant versus placebo

Study 2

Study 2 was a double-blind, placebo-controlled, crossover study conducted at 62 centers in Europe comparing KEPPRA 1000 mg/day (N=106), KEPPRA 2000 mg/day (N=105), and placebo (N=111) given in equally divided doses twice daily.

The first period of the study (Period A) was designed to be analyzed as a parallel-group study. After a prospective baseline period of up to 12 weeks, patients were randomized to one of the three treatment groups described above. The 16-week treatment period consisted of the 4-week titration period followed by a 12-week fixed dose evaluation period, during which concomitant AED regimens were held constant. The primary measure of effectiveness was a between group comparison of the percent reduction in weekly partial seizure frequency relative to placebo over the entire randomized treatment period (titration + evaluation period). Secondary outcome variables included the responder rate (incidence of patients with ≥50% reduction from baseline in partial-onset seizure frequency). The results of the analysis of Period A are displayed in Table 11.

Table 11: Reduction in Mean Over Placebo in Weekly Frequency of Partial-Onset Seizures in Study 2: Period A
 | Placebo (N=111) | KEPPRA 1000 mg/day (N=106) | KEPPRA 2000 mg/day (N=105)
Percent reduction in partial seizure frequency over placebo | – | 17.1% [statistically significant versus placebo] | 21.4%

The percentage of patients (y-axis) who achieved ≥50% reduction in weekly seizure rates from baseline in partial-onset seizure frequency over the entire randomized treatment period (titration + evaluation period) within the three treatment groups (x-axis) is presented in Figure 2.

Figure 2: Responder Rate (≥50% Reduction from Baseline) in Study 2: Period A

* statistically significant versus placebo

The comparison of KEPPRA 2000 mg/day to KEPPRA 1000 mg/day for responder rate was statistically significant (P=0.02). Analysis of the trial as a cross-over yielded similar results.

Study 3

Study 3 was a double-blind, placebo-controlled, parallel-group study conducted at 47 centers in Europe comparing KEPPRA 3000 mg/day (N=180) and placebo (N=104) in patients with refractory partial-onset seizures, with or without secondary generalization, receiving only one concomitant AED. Study drug was given in two divided doses. After a prospective baseline period of 12 weeks, patients were randomized to one of two treatment groups described above. The 16-week treatment period consisted of a 4-week titration period, followed by a 12-week fixed dose evaluation period, during which concomitant AED doses were held constant. The primary measure of effectiveness was a between group comparison of the percent reduction in weekly seizure frequency relative to placebo over the entire randomized treatment period (titration + evaluation period). Secondary outcome variables included the responder rate (incidence of patients with ≥50% reduction from baseline in partial-onset seizure frequency). Table 12 displays the results of the analysis of Study 3.

Table 12: Reduction in Mean Over Placebo in Weekly Frequency of Partial-Onset Seizures in Study 3
 | Placebo (N=104) | KEPPRA 3000 mg/day (N=180)
Percent reduction in partial seizure frequency over placebo | – | 23.0% [statistically significant versus placebo]

The percentage of patients (y-axis) who achieved ≥50% reduction in weekly seizure rates from baseline in partial-onset seizure frequency over the entire randomized treatment period (titration + evaluation period) within the two treatment groups (x-axis) is presented in Figure 3.

Figure 3: Responder Rate (≥50% Reduction from Baseline) in Study 3

* statistically significant versus placebo

Effectiveness in Partial-Onset Seizures in Pediatric Patients 4 Years to 16 Years of Age

Study 4 was a multicenter, randomized double-blind, placebo-controlled study, in pediatric patients 4 to 16 years of age with partial seizures uncontrolled by standard antiepileptic drugs (AEDs). Study 4 was conducted at 60 sites in North America. The study consisted of an 8-week baseline period and 4-week titration period followed by a 10-week evaluation period. Eligible patients who still experienced, on a stable dose of 1-2 AEDs, at least 4 partial-onset seizures during the 4 weeks prior to screening, as well as at least 4 partial-onset seizures in each of the two 4-week baseline periods, were randomized to receive either KEPPRA or placebo. Dosing was initiated at a dose of 20 mg/kg/day in two divided doses. During the treatment period, KEPPRA doses were adjusted in 20 mg/kg/day increments, at 2-week intervals to the target dose of 60 mg/kg/day. The primary measure of efficacy was a between group comparison of the percent reduction in weekly partial seizure frequency relative to placebo over the entire 14-week randomized treatment period (titration + evaluation period). Secondary outcome variables included the responder rate (incidence of patients with ≥ 50% reduction from baseline in partial-onset seizure frequency per week). The enrolled population included 198 patients (KEPPRA N=101, placebo N=97) with refractory partial-onset seizures, whether or not secondarily generalized. Table 13 displays the results of Study 4.

Table 13: Reduction in Mean Over Placebo in Weekly Frequency of Partial-Onset Seizures in Study 4
 | Placebo (N=97) | KEPPRA (N=101)
Percent reduction in partial seizure frequency over placebo | - | 26.8% [statistically significant versus placebo]

The percentage of patients (y-axis) who achieved ≥ 50% reduction in weekly seizure rates from baseline in partial-onset seizure frequency over the entire randomized treatment period (titration + evaluation period) within the two treatment groups (x-axis) is presented in Figure 4.

Figure 4: Responder Rate (≥ 50% Reduction from Baseline) in Study 4

*statistically significant versus placebo

Effectiveness in Partial-Onset Seizures in Pediatric Patients 1 Month to <4 Years of Age

Study 5 was a multicenter, randomized double-blind, placebo-controlled study, in pediatric patients 1 month to less than 4 years of age with partial seizures, uncontrolled by standard epileptic drugs (AEDs). Study 5 was conducted at 62 sites in North America, South America, and Europe. Study 5 consisted of a 5-day evaluation period, which included a 1-day titration period followed by a 4-day maintenance period. Eligible patients who experienced, on a stable dose of 1-2 AEDs, at least 2 partial-onset seizures during the 48-hour baseline video EEG were randomized to receive either KEPPRA or placebo. Randomization was stratified by age range as follows: 1 month to less than 6 months of age (N=4 treated with KEPPRA), 6 months to less than 1 year of age (N=8 treated with KEPPRA), 1 year to less than 2 years of age (N=20 treated with KEPPRA), and 2 years to less than 4 years of age (N=28 treated with KEPPRA). KEPPRA dosing was determined by age and weight as follows: children 1 month to less than 6 months old were randomized to a target dose of 40 mg/kg/day, and children 6 months to less than 4 years old were randomized to a target dose of 50 mg/kg/day. The primary measure of efficacy was the responder rate (percent of patients with ≥ 50% reduction from baseline in average daily partial-onset seizure frequency) assessed by a blinded central reader using a 48-hour video EEG performed during the last two days of the 4-day maintenance period. The enrolled population included 116 patients (KEPPRA N=60, placebo N=56) with refractory partial-onset seizures, whether or not secondarily generalized. A total of 109 patients were included in the efficacy analysis. A statistically significant difference between KEPPRA and placebo was observed in Study 5 (see Figure 5). The treatment effect associated with KEPPRA was consistent across age groups.

Figure 5: Responder Rate for All Patients Ages 1 Month to < 4 Years (≥ 50% Reduction from Baseline) in Study 5

*statistically significant versus placebo

14.2 Myoclonic Seizures in Patients with Juvenile Myoclonic Epilepsy

The effectiveness of KEPPRA as adjunctive therapy in patients 12 years of age and older with juvenile myoclonic epilepsy (JME) experiencing myoclonic seizures was established in one multicenter, randomized, double-blind, placebo-controlled study (study 6), conducted at 37 sites in 14 countries. Eligible patients on a stable dose of 1 antiepileptic drug (AED) experiencing one or more myoclonic seizures per day for at least 8 days during the prospective 8-week baseline period were randomized to either KEPPRA or placebo (KEPPRA N=60, placebo N=60). Patients were titrated over 4 weeks to a target dose of 3000 mg/day and treated at a stable dose of 3000 mg/day over 12 weeks (evaluation period). Study drug was given in 2 divided doses. The primary measure of efficacy was the proportion of patients with at least 50% reduction in the number of days per week with one or more myoclonic seizures during the treatment period (titration + evaluation periods) as compared to baseline. Table 14 displays the results for the 113 patients with JME in this study.

Table 14: Responder Rate (≥50% Reduction from Baseline) in Myoclonic Seizure Days per Week in Study 6
 | Placebo (N=59) | KEPPRA (N=54)
Percentage of responders | 23.7% | 60.4% [statistically significant versus placebo]

14.3 Primary Generalized Tonic-Clonic Seizures

The effectiveness of KEPPRA as adjunctive therapy in patients 6 years of age and older with idiopathic generalized epilepsy experiencing primary generalized tonic-clonic (PGTC) seizures was established in one multicenter, randomized, double-blind, placebo-controlled study (study 7), conducted at 50 sites in 8 countries. Eligible patients on a stable dose of 1 or 2 antiepileptic drugs (AEDs) experiencing at least 3 PGTC seizures during the 8-week combined baseline period (at least one PGTC seizure during the 4 weeks prior to the prospective baseline period and at least one PGTC seizure during the 4-week prospective baseline period) were randomized to either KEPPRA or placebo. The 8-week combined baseline period is referred to as "baseline" in the remainder of this section. Patients were titrated over 4 weeks to a target dose of 3000 mg/day for adults or a pediatric target dose of 60 mg/kg/day and treated at a stable dose of 3000 mg/day (or 60 mg/kg/day for children) over 20 weeks (evaluation period). Study drug was given in 2 equally divided doses per day. The primary measure of efficacy was the percent reduction from baseline in weekly PGTC seizure frequency for KEPPRA and placebo treatment groups over the treatment period (titration + evaluation periods). The population included 164 patients (KEPPRA N=80, placebo N=84) with idiopathic generalized epilepsy (predominately juvenile myoclonic epilepsy, juvenile absence epilepsy, childhood absence epilepsy, or epilepsy with Grand Mal seizures on awakening) experiencing primary generalized tonic-clonic seizures. Each of these syndromes of idiopathic generalized epilepsy was well represented in this patient population.

There was a statistically significant decrease from baseline in PGTC frequency in the KEPPRA-treated patients compared to the placebo-treated patients in Study 7 (see Table 15).

Table 15: Median Percent Reduction from Baseline in PGTC Seizure Frequency per Week in Study 7
 | Placebo (N=84) | KEPPRA (N=78)
Percentage reduction in PGTC seizure frequency | 44.6% | 77.6% [statistically significant versus placebo]

The percentage of patients (y-axis) who achieved ≥50% reduction in weekly seizure rates from baseline in PGTC seizure frequency over the entire randomized treatment period (titration + evaluation period) within the two treatment groups (x-axis) is presented in Figure 6.

Figure 6: Responder Rate (≥50% Reduction from Baseline) in PGTC Seizure Frequency per Week in Study 7

* statistically significant versus placebo

16 HOW SUPPLIED/STORAGE AND HANDLING

16.1 How Supplied

KEPPRA (levetiracetam) 500 mg/5 mL injection is a clear, colorless, sterile solution. It is supplied in single-use 5 mL vials, available in cartons of 10 vials (NDC 50474-002-63).

16.2 Storage

Store at 25°C (77°F); excursions permitted to 15°C to 30°C (59°F to 86°F) [see USP Controlled Room Temperature].

17 PATIENT COUNSELING INFORMATION

Psychiatric Reactions and Changes in Behavior

Advise patients and their caregivers that KEPPRA may cause changes in behavior (e.g., aggression, agitation, anger, anxiety, apathy, depression, hostility, and irritability) and psychotic symptoms [see Warnings and Precautions (5.1)] .

Effects on Driving or Operating Machinery

Inform patients that KEPPRA may cause dizziness and somnolence. Inform patients not to drive or operate machinery until they have gained sufficient experience on KEPPRA to gauge whether it adversely affects their ability to drive or operate machinery [see Warnings and Precautions (5.2)] .

Anaphylaxis and Angioedema

Advise patients to discontinue KEPPRA and seek medical care if they develop signs and symptoms of anaphylaxis or angioedema [see Warnings and Precautions (5.3)].

Dermatological Adverse Reactions

Advise patients that serious dermatological adverse reactions have occurred in patients treated with KEPPRA and instruct them to call their physician immediately if a rash develops [see Warnings and Precautions (5.4)] .

DRESS/Multiorgan Hypersensitivity

Instruct patients and caregivers that a fever or rash associated with signs of other organ system involvement (e.g., lymphadenopathy, hepatic dysfunction) may be drug-related and should be reported to their healthcare provider immediately. KEPPRA should be discontinued immediately if a serious hypersensitivity reaction is suspected [see Warnings and Precautions (5.5)].

Withdrawal of KEPPRA

Advise patients and caregivers not to discontinue use of KEPPRA without consulting with their healthcare provider. KEPPRA should normally be gradually withdrawn to reduce the potential of increased seizure frequency and status epilepticus [see Warnings and Precautions (5.7)].

Pregnancy

Advise patients to notify their healthcare provider if they become pregnant or intend to become pregnant during KEPPRA therapy. Encourage patients to enroll in the North American Antiepileptic Drug (NAAED) pregnancy registry if they become pregnant [see Use in Specific Populations (8.1)] .

KEPPRA injection manufactured for
UCB, Inc.
Smyrna, GA 30080

KEPPRA is a registered trademark of the UCB Group of Companies
© 2024, UCB, Inc., Smyrna, GA 30080
All rights reserved.

PRINCIPAL DISPLAY PANEL - 5 mL Vial Carton

NDC 50474-002-63
10 single-use 5 mL vials

Keppra®
(levetiracetam) injection
500 mg/5 mL
(100 mg/mL)

Rx only

FOR INTRAVENOUS USE ONLY
MUST BE DILUTED PRIOR TO ADMINISTRATION